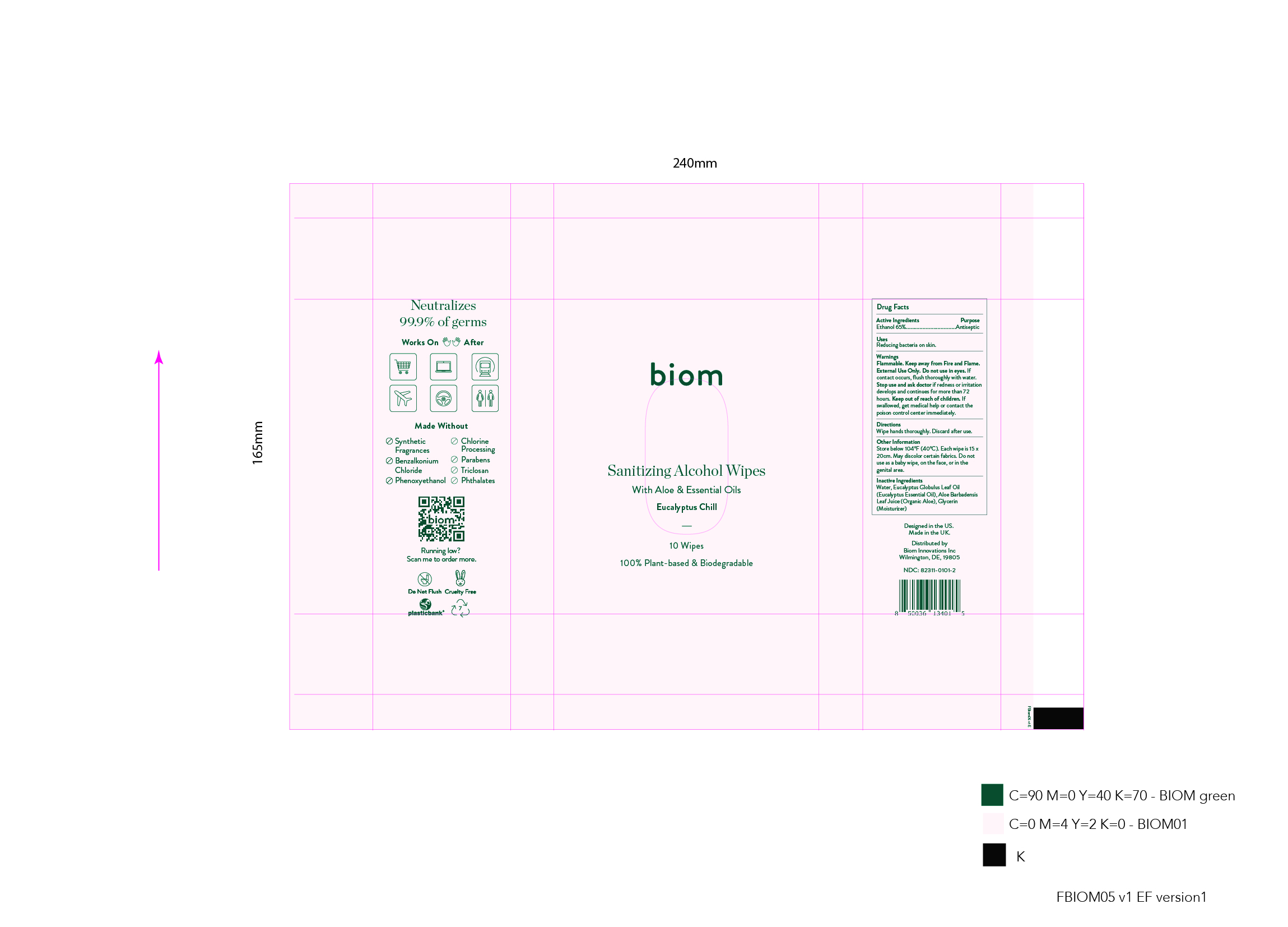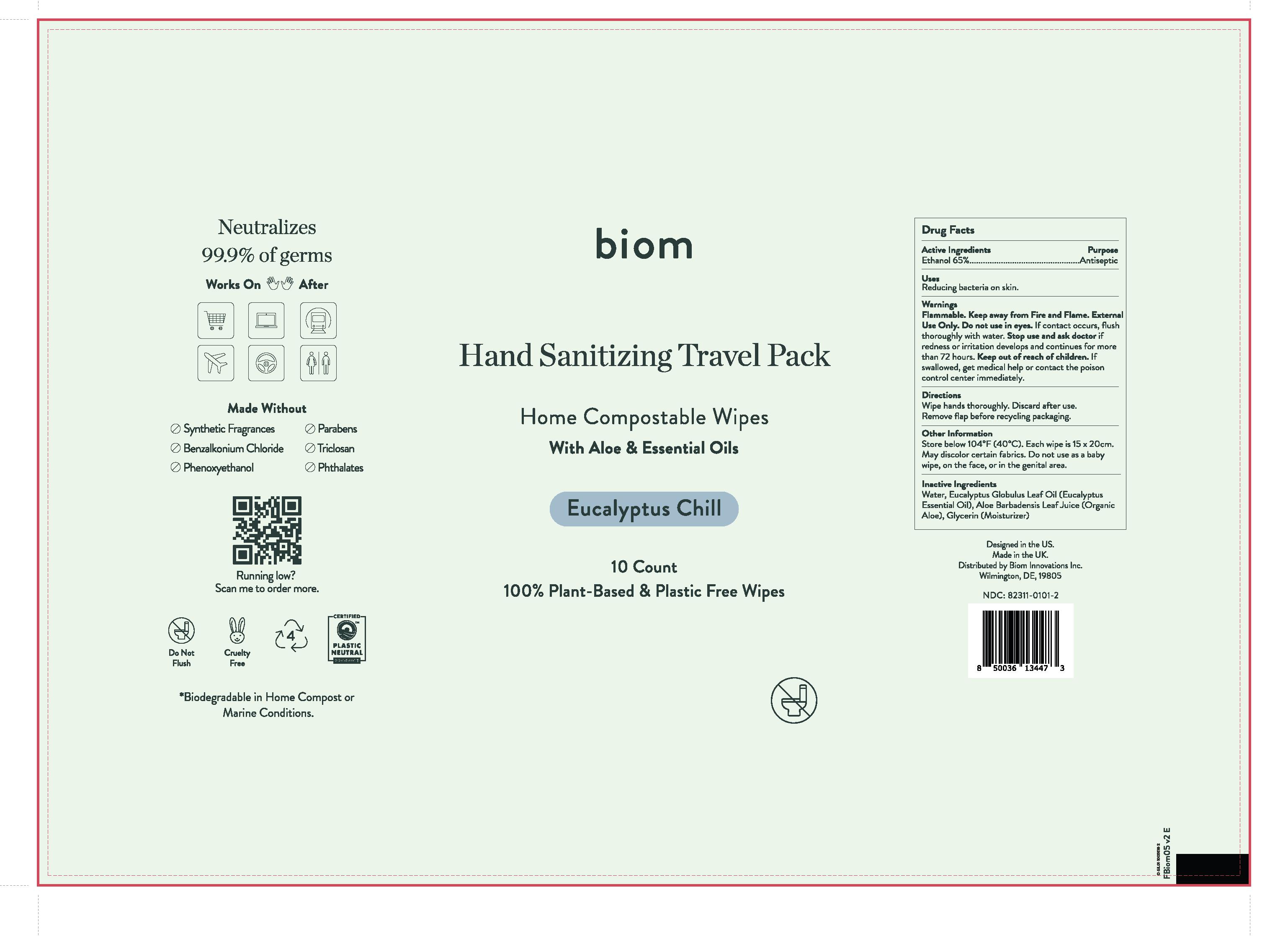 DRUG LABEL: biom Sanitizing Alcohol Wipes - Eucalyptus Chill
NDC: 82311-0101 | Form: SWAB
Manufacturer: Biom Innovations Inc
Category: otc | Type: HUMAN OTC DRUG LABEL
Date: 20241224

ACTIVE INGREDIENTS: ALCOHOL 184.1 mL/263 mL
INACTIVE INGREDIENTS: EUCALYPTUS GLOBULUS LEAF 0.1315 mL/263 mL; ALOE VERA LEAF 2.63 mL/263 mL; GLYCERIN 2.64315 mL/263 mL; WATER 73.49535 mL/263 mL

[biom05] Sanitizing Alcohol Wipes - Eucalyptus Chill - 10 wipes

This hand sanitizer (65%(w/w) ethanol in an aqueous solution):

- Is manufactured using United States Pharmacopoeia (USP) grade ingredients.

- The alcohol (ethanol) is (USP or Food Chemical Codex (FCC) grade), and is denatured according to Alcohol & Tobacco Tax and Trade Bureau regulations in 27 CFR part 20.

Active Ingredient(s)

Alcohol 65% w/w. Purpose: Antiseptic

Purpose

Reducing bacteria on skin.

Directions

Wipe hands thoroughly. Discard after use.

Dosage and Administration

Ethanol 65%. Wipe hands thoroughly. Discard after use.

Warnings

Flammable. Keep away from Fire and Flame. External Use Only. Do not use in eyes. If contact occurs, flush thoroughly with water. Stop use and ask doctor if redness or irritation develops and continues for more than 72 hours. Keep out of reach of children. If swallowed, get medical help or contact the poison control center immediately.

Keep out of reach of children. If swallowed, get medical help or contact the poison control center immediately.

Other information

Store below 104° F (40° C).
Each wipe is 15 x 20 cm.
May discolor certain fabrics.
Do not use as a baby wipe, on
the face, or in the genital area.

Inactive ingredients

Water, Eucalyptus Globulus Leaf Oil (Eucalyptus Essential Oil), Aloe Barbadensis Leaf Juice (Organic Aloe), Glycerin (Moisturizer)

Package Label - Principal Display Panel

10 wipes; NDC82311-0101-2